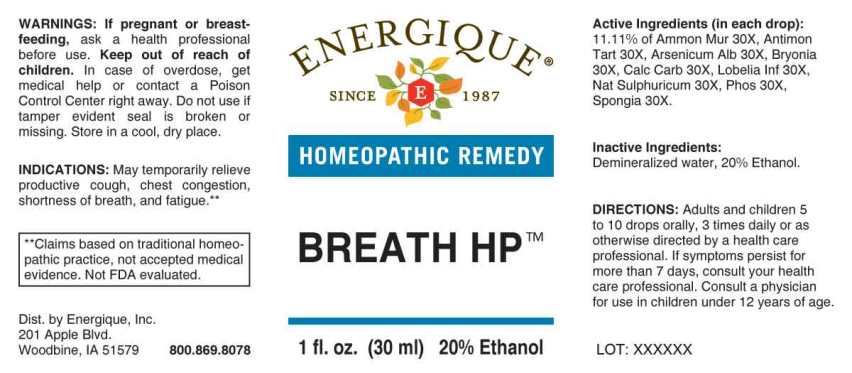 DRUG LABEL: Breath HP
NDC: 44911-0591 | Form: LIQUID
Manufacturer: Energique, Inc.
Category: homeopathic | Type: HUMAN OTC DRUG LABEL
Date: 20240723

ACTIVE INGREDIENTS: AMMONIUM CHLORIDE 30 [hp_X]/1 mL; ANTIMONY POTASSIUM TARTRATE 30 [hp_X]/1 mL; ARSENIC TRIOXIDE 30 [hp_X]/1 mL; BRYONIA ALBA ROOT 30 [hp_X]/1 mL; OYSTER SHELL CALCIUM CARBONATE, CRUDE 30 [hp_X]/1 mL; LOBELIA INFLATA WHOLE 30 [hp_X]/1 mL; SODIUM SULFATE 30 [hp_X]/1 mL; PHOSPHORUS 30 [hp_X]/1 mL; SPONGIA OFFICINALIS SKELETON, ROASTED 30 [hp_X]/1 mL
INACTIVE INGREDIENTS: WATER; ALCOHOL

DRUG FACTS:

ACTIVE INGREDIENTS:

(in each drop): 11.11% of Ammonium Muriaticum 30X, Antimonium Tartaricum 30X, Arsenicum Album 30X, Bryonia (Alba) 30X, Calcarea Carbonica 30X, Lobelia Inflata 30X, Natrum Sulphuricum 30X, Phosphorus 30X, Spongia Tosta 30X.

INDICATIONS:

May temporarily relieve productive cough, chest congestion, shortness of breath and Fatigue.**

**Claims based on traditional homeopathic practice, not accepted medical evidence. Not FDA evaluated.

WARNINGS:

If pregnant or breast-feeding, ask a health professional before use.

Keep out of reach of children. In case of overdose, get medical help or contact a Poison Control Center right away.

Do not use if tamper evident seal is broken or missing.

Store in a cool, dry place.

KEEP OUT OF REACH OF CHILDREN:

In case of overdose, get medical help or contact a Poison Control Center right away.

DIRECTIONS:

Adults and children 5 to 10 drops orally, 3 times daily or as otherwise directed by a health care professional. If symptoms persist for more than 7 days, consult your health care professional.

Consult a physician for use in children under 12 years of age.

INDICATIONS:

May temporarily relieve productive cough, chest congestion, shortness of breath and Fatigue.**

**Claims based on traditional homeopathic practice, not accepted medical evidence. Not FDA evaluated.

INACTIVE INGREDIENTS:

Demineralized water, 20% Ethanol

QUESTIONS:

Dist. by Energique, Inc.

201 Apple Blvd

Woodbine, IA 51579 800-869-8078

PACKAGE LABEL DISPLAY:

ENERGIQUE
SINCE 1987
HOMEOPATHIC REMEDY
BREATH HP
1 fl. oz. (30 ml)